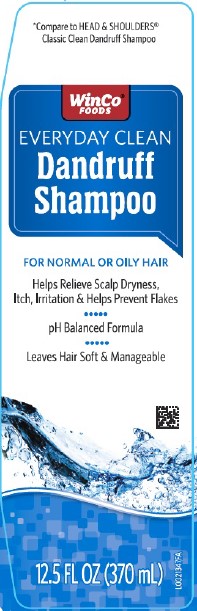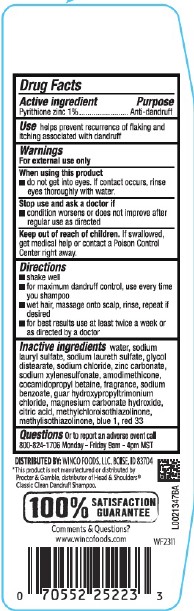 DRUG LABEL: Everyday Clean Dandruff
NDC: 67091-178 | Form: SHAMPOO
Manufacturer: WinCo Foods, LLC
Category: otc | Type: HUMAN OTC DRUG LABEL
Date: 20260212

ACTIVE INGREDIENTS: PYRITHIONE ZINC 10 mg/1 mL
INACTIVE INGREDIENTS: WATER; SODIUM LAURYL SULFATE; SODIUM LAURETH SULFATE; GLYCOL DISTEARATE; SODIUM CHLORIDE; ZINC CARBONATE; SODIUM XYLENESULFONATE; AMODIMETHICONE (800 CST); COCAMIDOPROPYL BETAINE; SODIUM BENZOATE; GUAR HYDROXYPROPYLTRIMONIUM CHLORIDE (1.7 SUBSTITUENTS PER SACCHARIDE); MAGNESIUM CARBONATE HYDROXIDE; CITRIC ACID MONOHYDRATE; METHYLCHLOROISOTHIAZOLINONE; METHYLISOTHIAZOLINONE; FD&C BLUE NO. 1; D&C RED NO. 33

WinCo 153.008/153BC
Everyday Clean Dandruff Shampoo

Active ingredient

Pyrithione zinc 1%

Purpose

Anti-dandruff

Use

helps prevent recurrence of flaking and itching associated with dandruff

Warnings

For external use only

When using this product

- do not get into eyes. If contact occurs, rinse eyes thoroughly with water.

Stop use and ask a doctor if

- Condition worsens or does not improve after regular use as directed

Keep out of reach of children.

If swallowed, get medical help or contact a Poison Control Center right away.

Directions

- shake well
- for maximum dandruff control, use every time you shampoo
- wet hair, massage onto scalp, rinse, repeat if desired
- for best results use at least twice a week or as directed by a doctor

Inactive ingredients

water, sodium lauryl sulfate, sodium laureth sulfate, glycol distearate, sodium chloride, zinc carbonate, sodium xylenesulfonate, amodimethicone, cocamidopropyl betaine, fragrance, sodium benzoate, guar hydroxypropyltrimonium chloride, magnesium carbonate hydroxide, citric acid, methylchloroisothiazolinone, methylisothiazolinone, blue 1, red 33

Questions

Or to report and adverse event call 800-824-1706 Monday-Friday 9 am-4pm MST

Adverse Reaction

DISTRIBUTED BY: WINCO FOODS, LLC, BOISE, ID 83704

*This product is not manufatured or distributed by Procter & Gamble, distributor of Head & Shoulders® Classic Clean Dandruff Shampoo.

100% SATISFACTION GUARANTEE

Comments & Questions?

www.wincofoods.com

Principal display panel

*Compare to HEAD & SHOULDERS®Classic Clean Dandruff Shampoo

WinCo®FOODS

EVERYDAY CLEAN

Dandruff Shampoo

FOR NORMAL OR OILY HAIR

Helps Relieve Scalp Dryness, Itch, Irritation & Helps Prevent Flakes

pH Balanced Formula

Leaves Hair Soft & Manageable

12.5 FL OZ (370 mL)